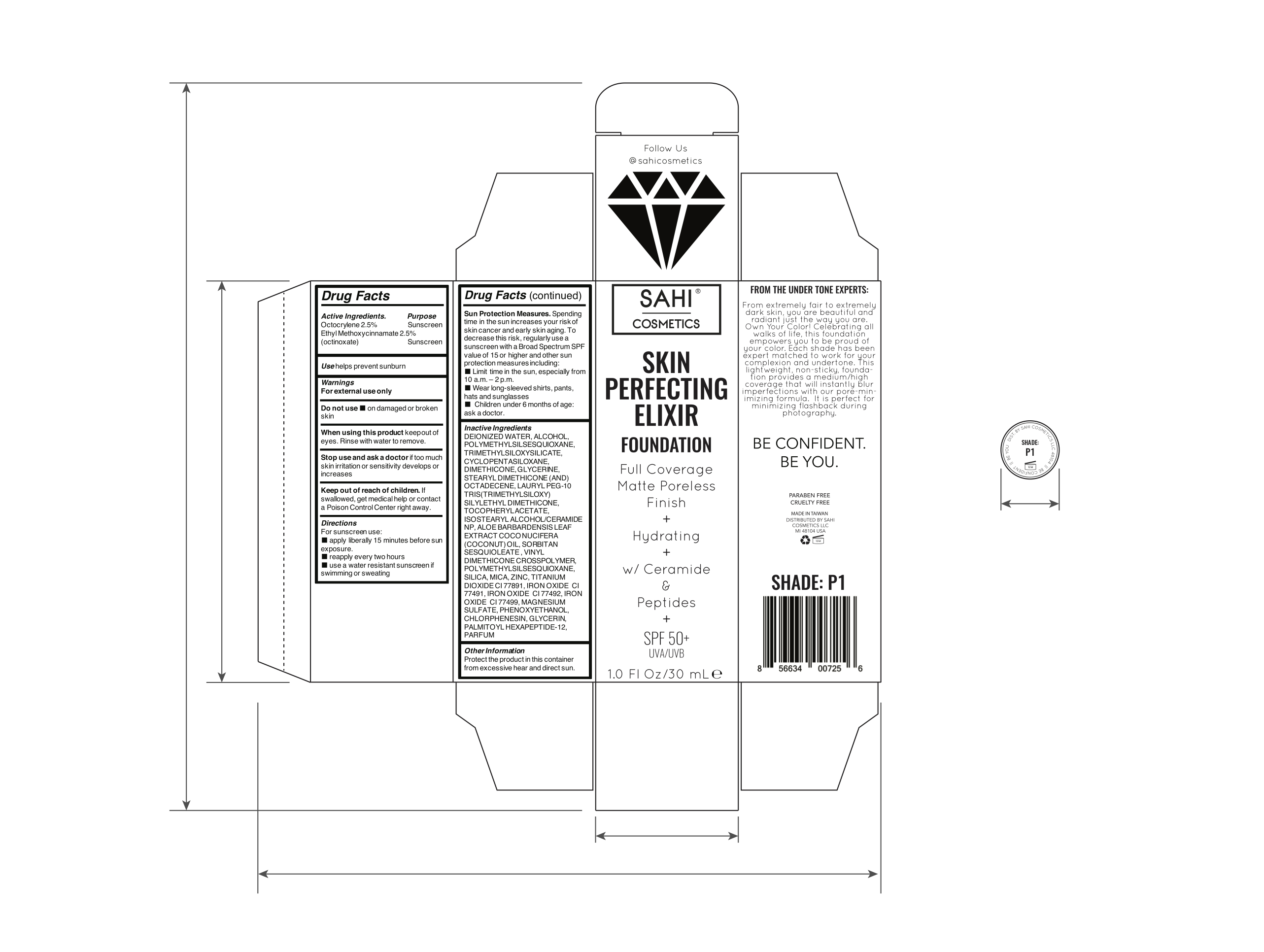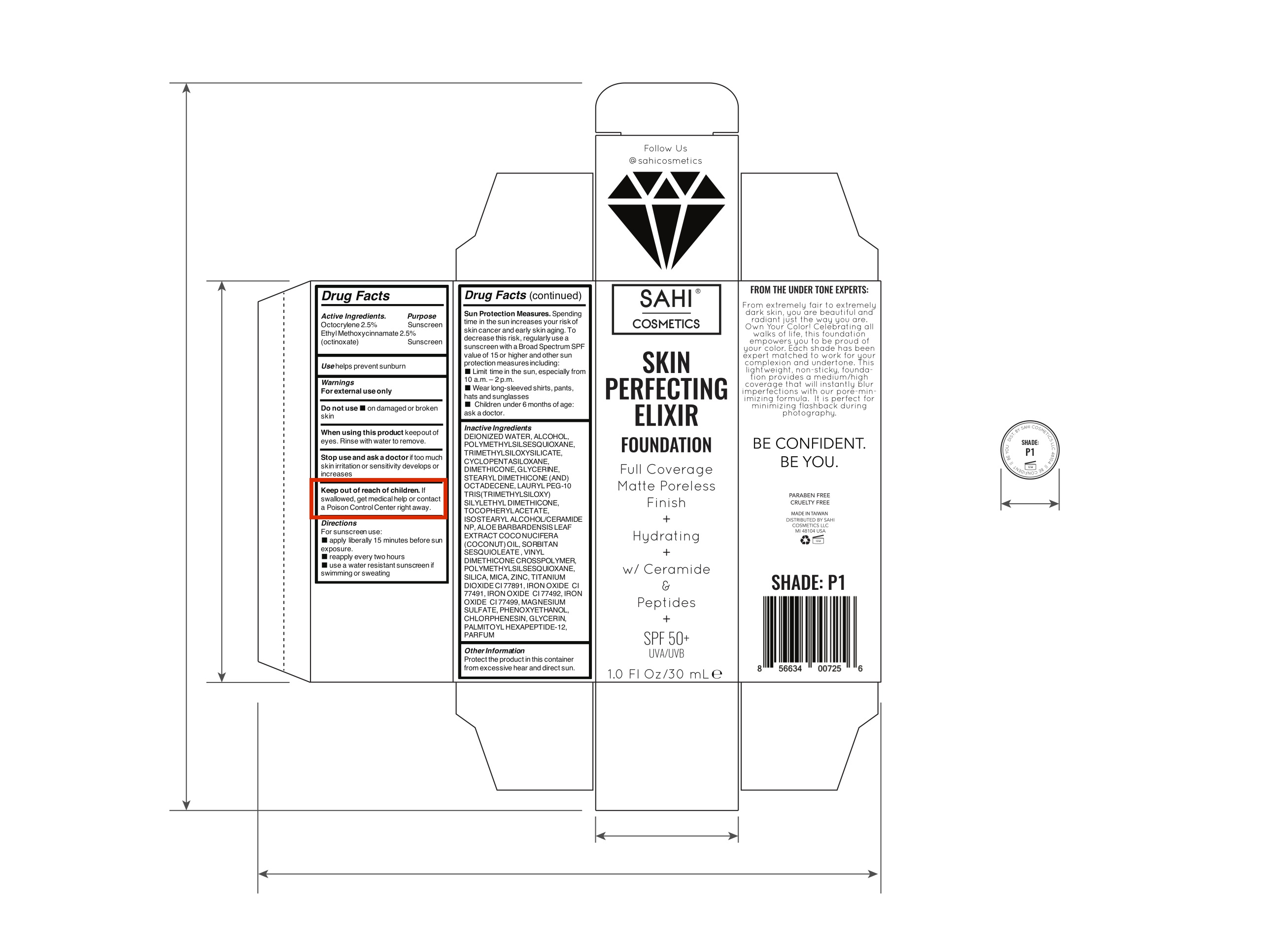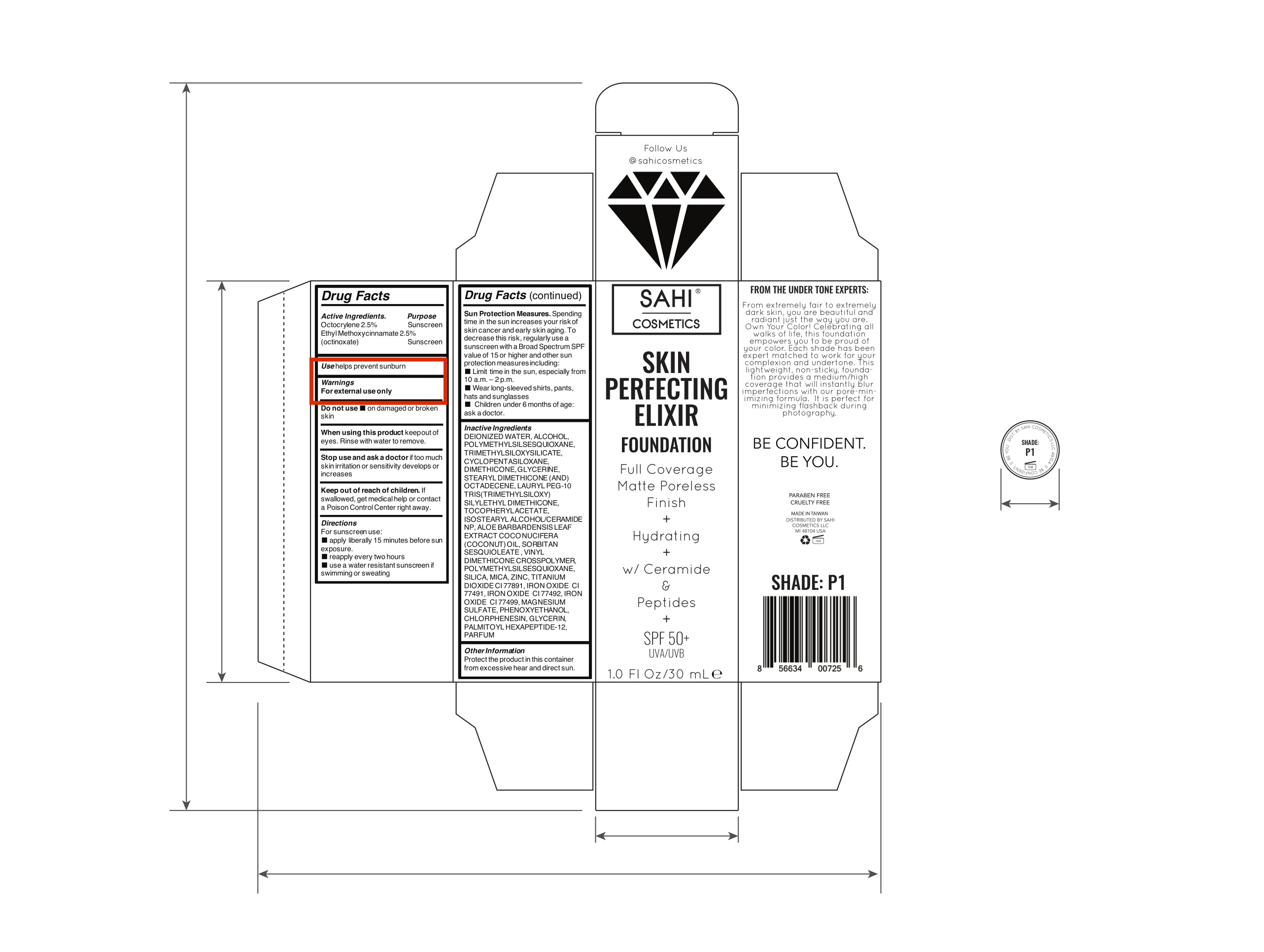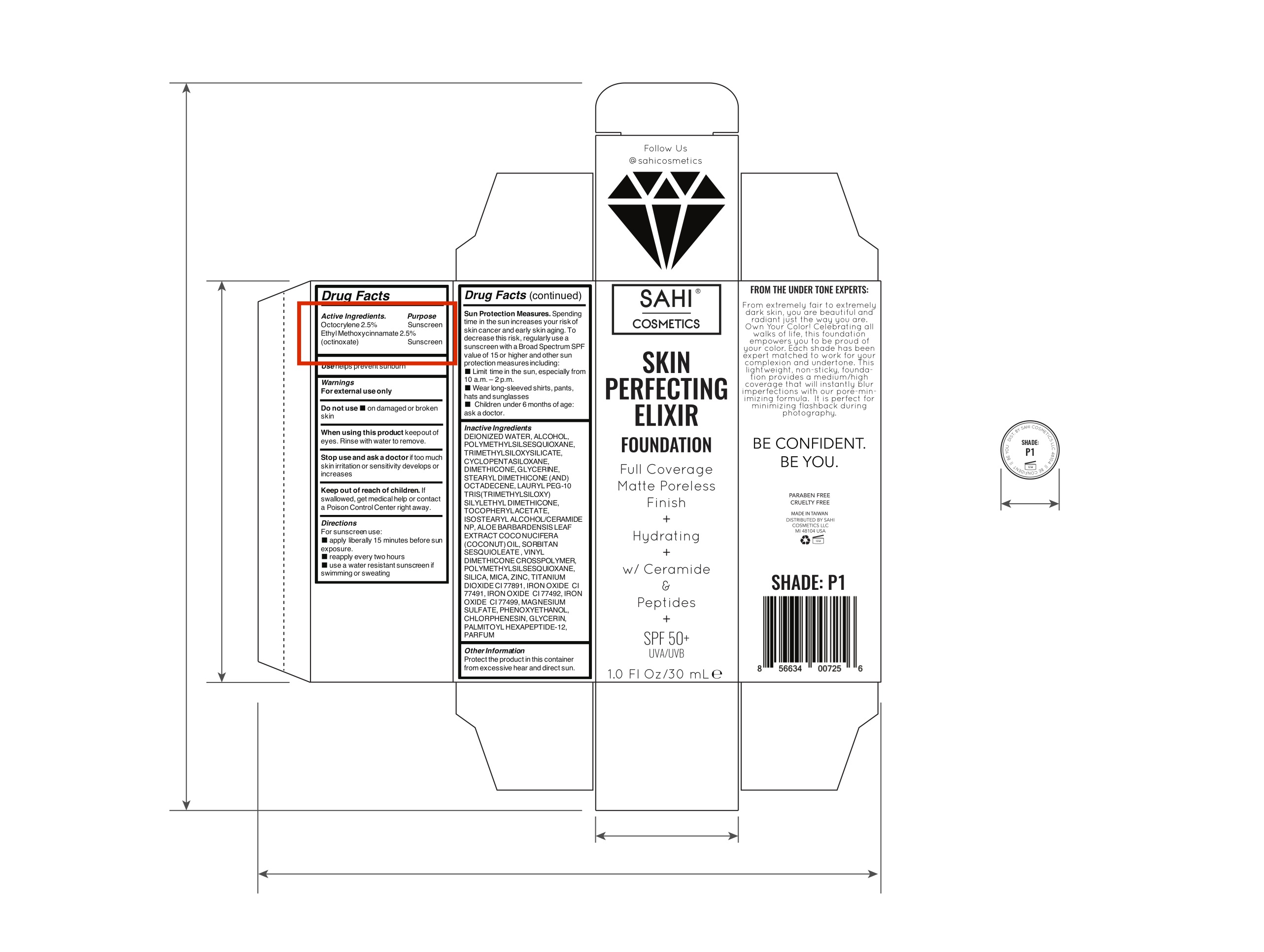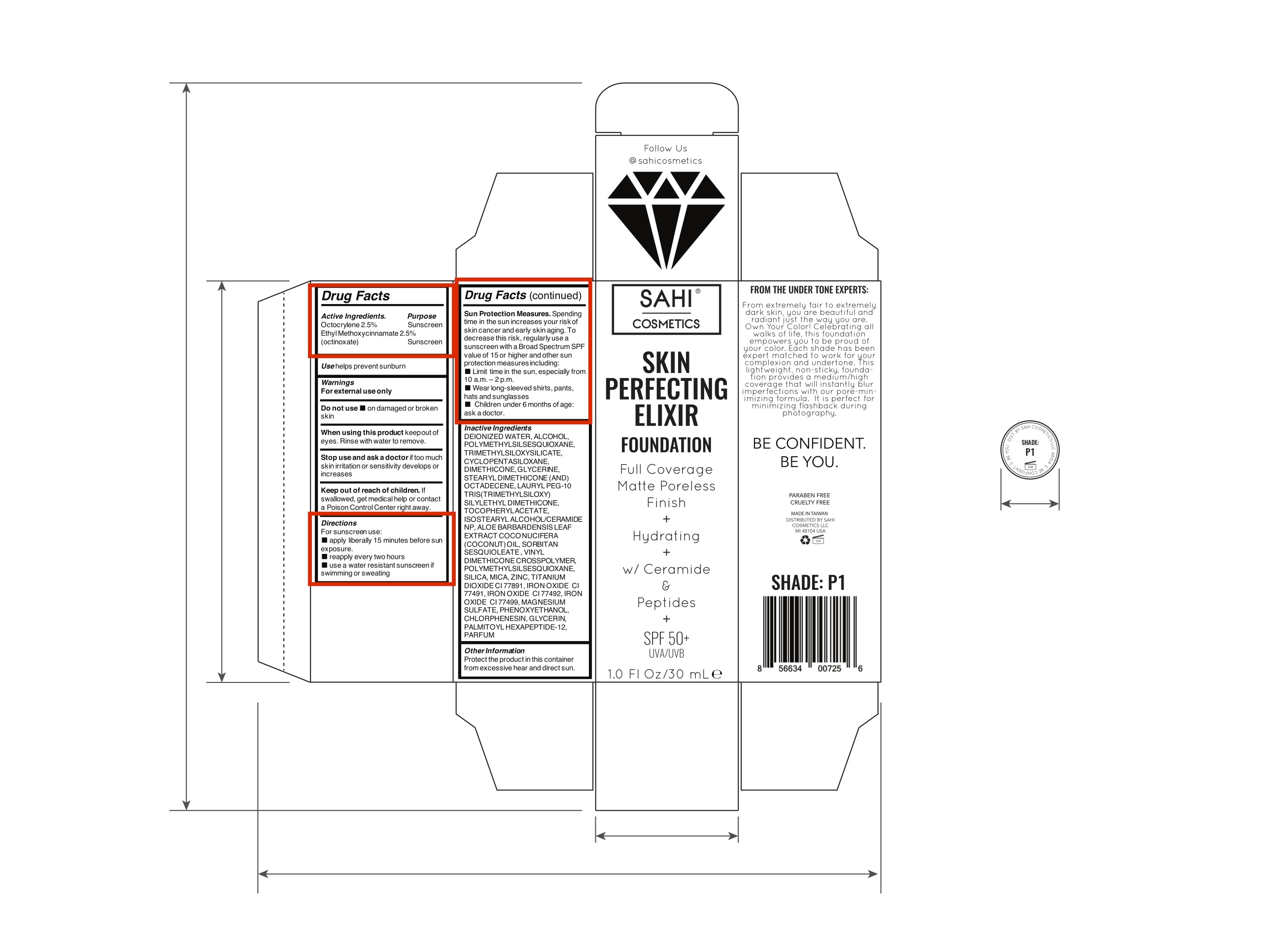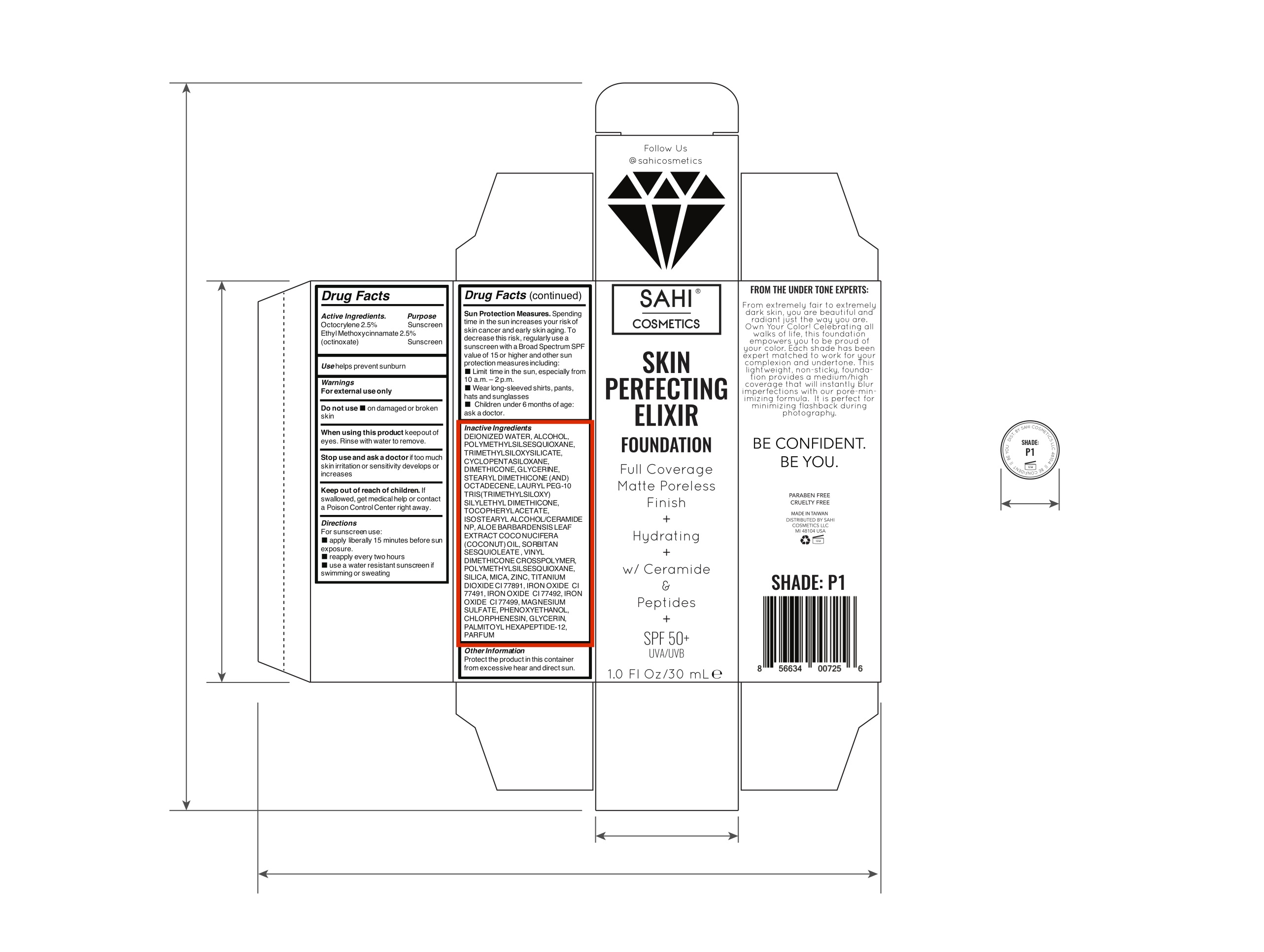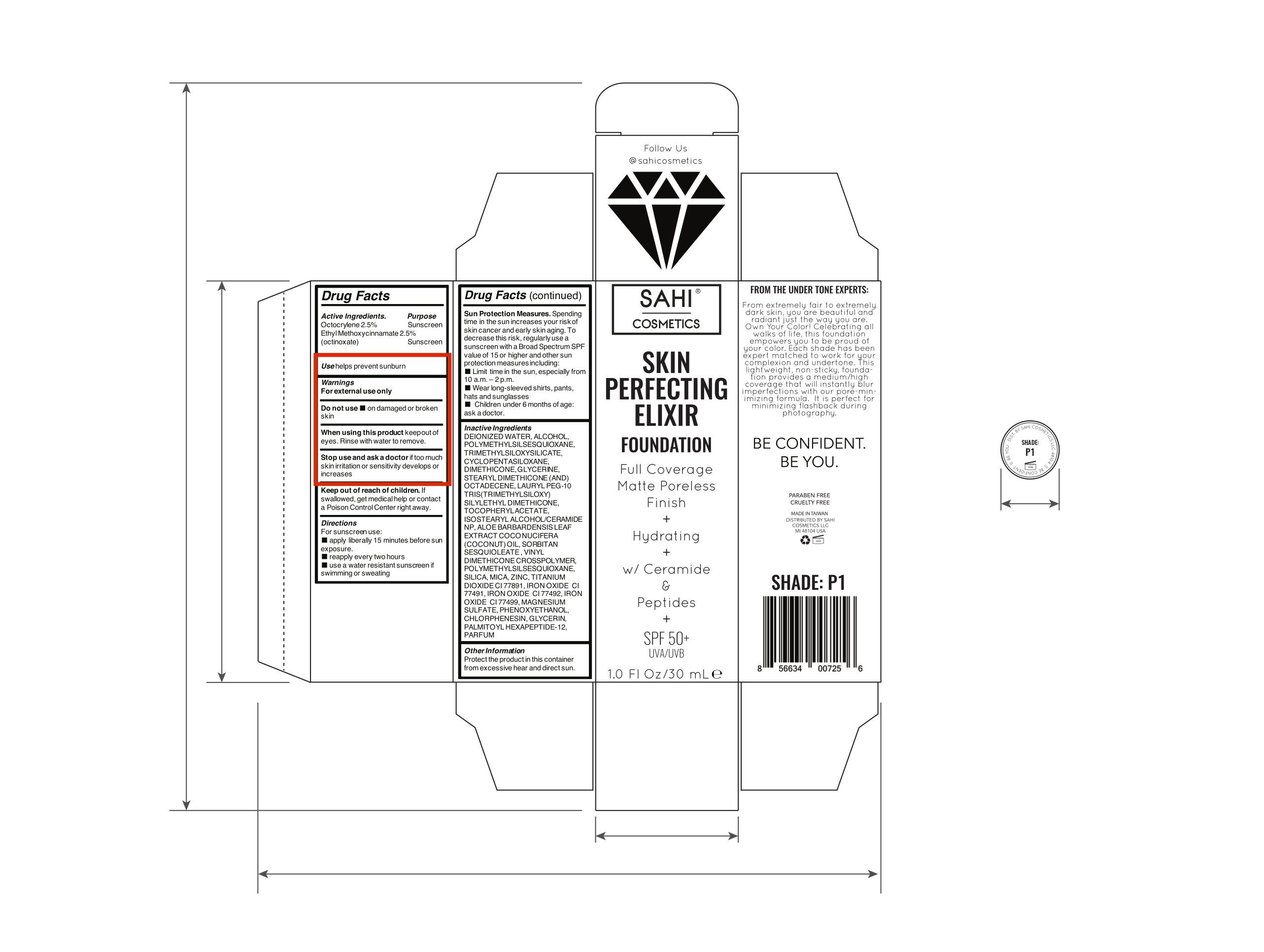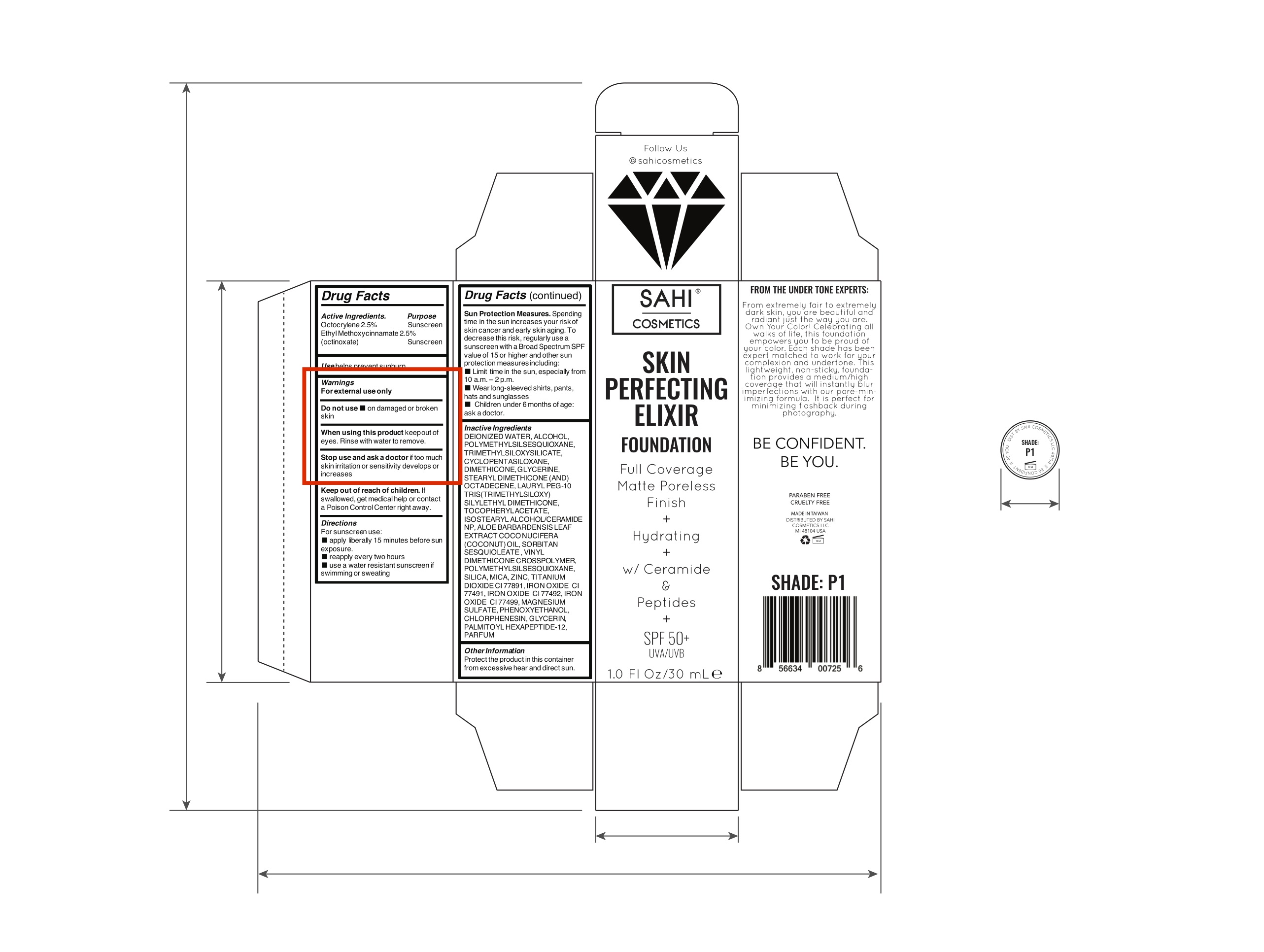 DRUG LABEL: Sahi Cosmetics
NDC: 72878-2530 | Form: LOTION
Manufacturer: SAHI Cosmetics L.L.C.
Category: otc | Type: HUMAN OTC DRUG LABEL
Date: 20210202

ACTIVE INGREDIENTS: OCTOCRYLENE 2.5 g/0.025 mL; OCTINOXATE 2.5 g/0.025 mL
INACTIVE INGREDIENTS: WATER 1 g/0.025 mL

Sahi Cosmetics Skin Perfecting Elixir Foundation

Drug Facts

Drug Facts Active Ingredients.

Purpose

Drug Facts (continued) Sun Protection Measures. Spending

time in the sun increases your risk of skin cancer and early skin aging. To decrease this risk, regularly use a sunscreen with a Broad Spectrum SPF value of 15 or higher and other sun protection measures including:

Octocrylene 2.5% Sunscreen
Ethyl Methoxycinnamate 2.5%

(octinoxate) Sunscreen
Use helps prevent sunburn

Warnings

For external use only

Limit time in the sun, especially from 10 a.m. – 2 p.m.

Wear long-sleeved shirts, pants, hats, and sunglasses

Do not use

Children under 6 months of age: askadoctor.

on damaged or broken

When using this product keepout of eyes. Rinse with water to remove.

Stop use and ask a doctor if too much skin irritation or sensitivity develops or increases

Keep out of reach of children. If swallowed, get medical help or contact a Poison Control Center right away.

Directions

For sunscreen use:
apply liberally 15 minutes before sun

skin

exposure.
reapply every two hours
use a water resistant sunscreen if swimming or sweating.

Inactive Ingredients

DEIONIZED WATER, ALCOHOL,
P O L Y M E T H Y L S I L S E S Q UI O X A N E ,
T RIMET HYLSILOXYSILIC A TE, CYCLOPENT ASILOXANE, DIMETHICONE,GLYCERINE, STEARYL DIMETHICONE (AND) OCT ADECENE, LAURYL PEG-10 TRIS(TRIMETHYLSILOXY) SILYLETHYL DIMETHICONE, TOCOPHERYL ACET ATE, ISOSTEARYL ALCOHOL/CERAMIDE NP, ALOE BARBARDENSIS LEAF EXTRACT COCO NUCIFERA (COCONUT) OIL, SORBIT AN SESQUIOLEATE , VINYL DIMETHICONE CROSSPOLYMER, P O L Y M E T H Y L S I L S E S Q UI O X A N E , SILICA, MICA, ZINC, TIT ANIUM DIOXIDECI77891,IRONOXIDE CI 77491,IRONOXIDE CI77492,IRON OXIDE CI77499,MAGNESIUM SULFATE, PHENOXYETHANOL, CHLORPHENESIN, GLYCERIN, PALMITOYL HEXAPEPTIDE-12, PARFUM

Other Information

Protect the product in this container from excessive hear and direct sun.